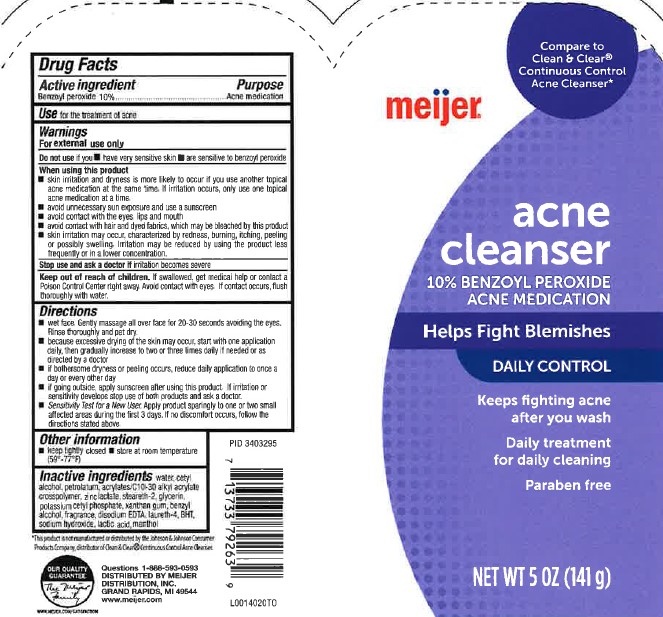 DRUG LABEL: Acne Cleanser
NDC: 41250-264 | Form: CREAM
Manufacturer: Meijer, Inc.
Category: otc | Type: HUMAN OTC DRUG LABEL
Date: 20260219

ACTIVE INGREDIENTS: BENZOYL PEROXIDE 100 mg/1 g
INACTIVE INGREDIENTS: WATER; CETYL ALCOHOL; PETROLATUM; CARBOMER INTERPOLYMER TYPE A (ALLYL SUCROSE CROSSLINKED); ZINC LACTATE; STEARETH-2; GLYCERIN; POTASSIUM CETYL PHOSPHATE; XANTHAN GUM; BENZYL ALCOHOL; EDETATE DISODIUM ANHYDROUS; LAURETH-4; BUTYLATED HYDROXYTOLUENE; SODIUM HYDROXIDE; LACTIC ACID; MENTHOL

Meijer 264.005/264AI rev 1-264AJ
Daily Acne Control Cleanser

Active ingredient

Benzoyl peroxide 10%

Purpose

Acne medication

use

for the treatment of acne

Warnings

For external use only

Do not use if you

- have very sensitive skin
- are sensitive to benzoyl peroxide

When using this product

- skin irritation and dryness is more likely to occur if you use another topical acne medication at the same time. If irritation occurs, only use one topical acne medication at a time.
- avoid unnecessary sun exposure and use a sunscreen
- avoid contact with the eyes, lips and mouth
- avoid contact with hair and dyed fabrics, which may be bleached by this product
- skin irritation may occur, characterized by redness, burning, itching, peeling or possible swelling. Irritation may be reduced by using the product less frequently or in a lower concentration

Stop use and ask a doctor if

irritation becomes severe

Keep out of reach of children.

If swallowed, get medical help or contact a Poison Control Center right away. Avoid contact with eyes. If contact occurs, flush thoroughly with water.

Directions

- wet face. Gently massage all over face for 20-30 seconds avoiding the eyes. Rinse thoroughly and pat dry.
- because excessive drying of the skin may occur, start with one application daily, then gradually increase to two or three times daily if needed or as directed by a doctor
- if bothersome dryness or peeling occurs, reduce daily application to once a day or every other day
- if going outside, apply sunscreen after using this product. If irritation or sensitivity develops stop use of both products and ask a doctor
- Sensitivity Test for a New User. Apply product sparingly to one or two small affected areas, during the first 3 days. If no discomfort occurs, follow the directions stated above.

Other information

- keep tightly closed
- store at room temperature (59⁰-77⁰)

Inactive ingredients

water, cetyl alcohol, petrolatum, acrylates/C10-30 alkyl acrylate crosspolymer, zinc lactate, steareth-2, glycerin, potassium cetyl phosphate, xanthan gum, benzyl alcohol, fragrance, disodium EDTA, laureth-4, BHT, sodium hydroxide, lactic acid, menthol

Disclaimer

*This product is not manufactured or distributed by Johnson & Johnson Consumer Products Company, distributor of Clean & Clear®Continuous Control Acne Cleanser.

ADVERSE REACTION

Questions 1-888-593-0593

DISTRIBUTED BY MEIJER DISTRIBUTION, INC

GRAND RAPIDS, MI 49544

www.meijer.com

OUR QUALITY GUARANTEE

The Meijer Family

www.meijer.com/satisfaction

PID 3403295

Principal display panel

Compare to CLEAN & CLEAR®Continuous Control Acne Cleanser*

meijer®

Acne

Cleanser

10% Benzoyl Peroside

Acne Medication

Helps Fight Blemishes

DAILY CONTROL

Keeps fighting Acne after you wash

Daily treatment for daily cleaning

Paraben free

NET WT 5 OZ (141 g)